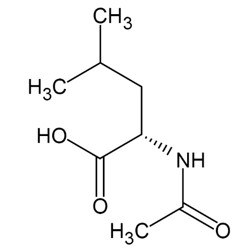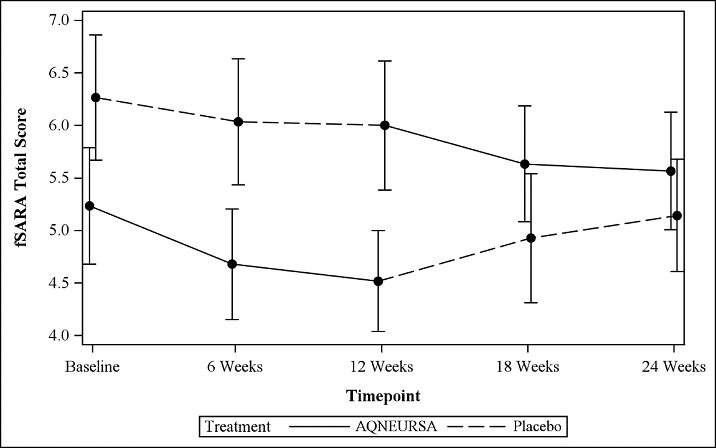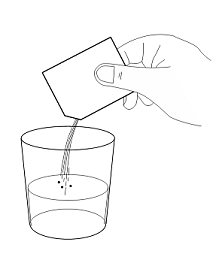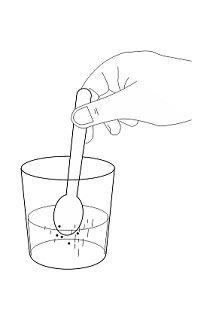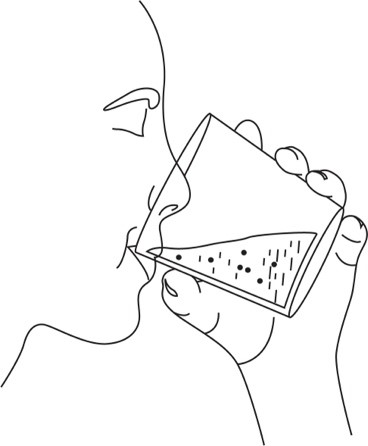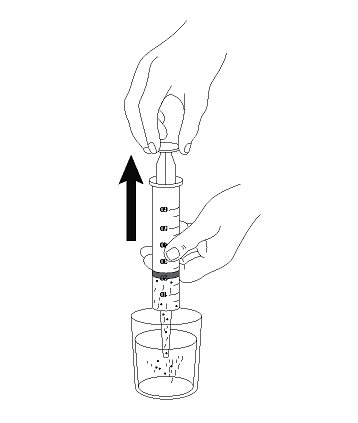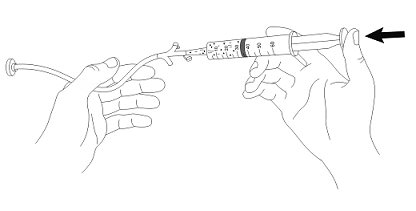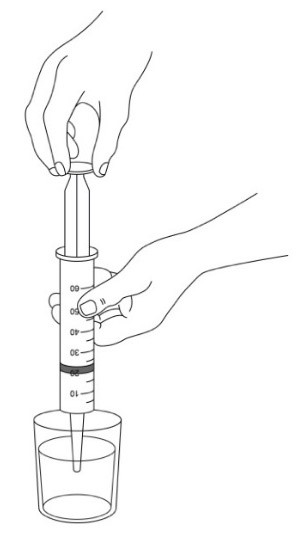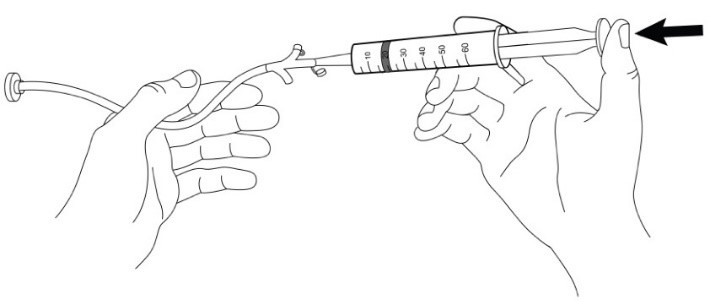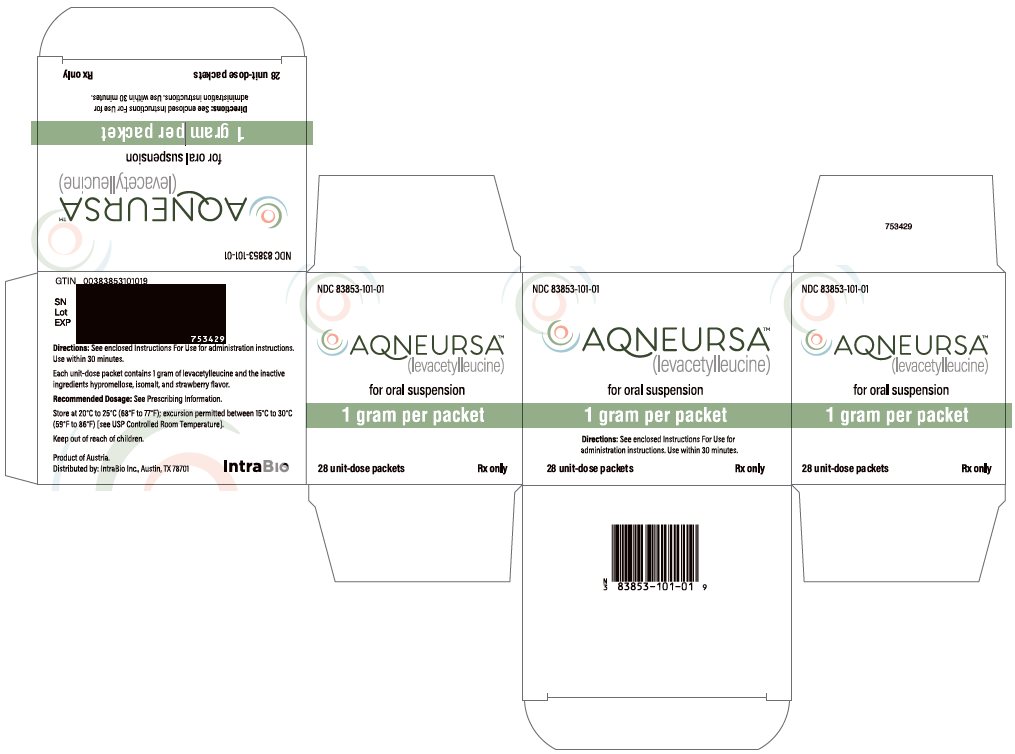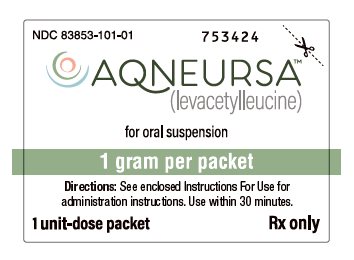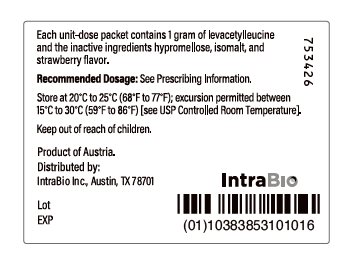 DRUG LABEL: AQNEURSA
NDC: 83853-101 | Form: GRANULE, FOR SUSPENSION
Manufacturer: IntraBio Inc
Category: prescription | Type: HUMAN PRESCRIPTION DRUG LABEL
Date: 20250123

ACTIVE INGREDIENTS: LEVACETYLLEUCINE 1000 mg/1 1

HIGHLIGHTS OF PRESCRIBING INFORMATION

These highlights do not include all the information needed to use AQNEURSA safely and effectively. See full prescribing information for AQNEURSA.
AQNEURSA™ (levacetylleucine) for oral suspension
Initial U.S. Approval: 2024

1 INDICATIONS AND USAGE

AQNEURSA is indicated for the treatment of neurological manifestations of Niemann-Pick disease type C (NPC) in adults and pediatric patients weighing ≥15 kg. (1)

2 DOSAGE AND ADMINISTRATION

- For females of reproductive potential, verify that the patient is not pregnant prior to initiating treatment. (2.1)
- Recommended dosage (2.2)

Patient Body Weight | Morning Dose | Afternoon Dose | Evening Dose
15 to <25 kg | 1 g | No Dose | 1 g
25 to <35 kg | 1 g | 1 g | 1 g
35 kg or more | 2 g | 1 g | 1 g

- See the full prescribing information for administration instructions. (2.3)

3 DOSAGE FORMS AND STRENGTHS

For oral suspension: 1 gram levacetylleucine in a unit-dose packet. (3)

4 CONTRAINDICATIONS

None. (4)

5 WARNINGS AND PRECAUTIONS

Embryo-Fetal Toxicity: May cause fetal harm. Advise females of reproductive potential to use effective contraception during treatment and for 7 days after the last dose if AQNEURSA is discontinued. (5.1)

6 ADVERSE REACTIONS

Most common adverse reactions (incidence ≥5% and greater than placebo) are abdominal pain, dysphagia, upper respiratory tract infections, and vomiting. (6)

To report SUSPECTED ADVERSE REACTIONS, contact IntraBio Inc. at 1-833-306-9677 or FDA at 1-800-FDA-1088 or www.fda.gov/medwatch.

7 DRUG INTERACTIONS

- N-acetyl-DL-leucine or N-acetyl-D-leucine: Avoid concomitant use with AQNEURSA. (7.1)
- P-glycoprotein (P-gp) Transporter Substrates: Monitor for adverse reactions if used with AQNEURSA. (7.2)

FULL PRESCRIBING INFORMATION

1 INDICATIONS AND USAGE

AQNEURSA™ is indicated for the treatment of neurological manifestations of Niemann-Pick disease type C (NPC) in adults and pediatric patients weighing ≥15 kg.

2 DOSAGE AND ADMINISTRATION

2.1 Important Recommendation Prior to AQNEURSA Treatment Initiation

For females of reproductive potential, verify that the patient is not pregnant [see Use in Specific Populations (8.1, 8.3)].

2.2 Recommended Dosage

The recommended dosage of AQNEURSA is based on the patient’s actual body weight (kg) to be administered orally up to three times daily. See Table 1.

AQNEURSA can be taken with or without food [see Clinical Studies (14)].

For 2 gram levacetylleucine doses, prepare two AQNEURSA packets individually [see Dosage and Administration (2.3)].

Table 1 Recommended Dosage of Levacetylleucine Based on Body Weight (kg)
Patient’s Body Weight | Morning Dose | Afternoon Dose | Evening Dose
15 kg to less than 25 kg | 1 gram | No Dose | 1 gram
25 kg to less than 35 kg | 1 gram | 1 gram | 1 gram
35 kg or more | 2 gram | 1 gram | 1 gram

One AQNEURSA packet contains 1 gram levacetylleucine.

Missed Dose

If a dose of AQNEURSA is missed, skip the missed dose and take the next dose at the scheduled time. Do not take 2 doses at the same time to make up for a missed dose.

2.3 Preparation and Administration Instructions

Oral Administration

For oral administration, administer AQNEURSA as follows:

1. Obtain the required number of AQNEURSA packets for the prescribed dose (one or two packets).
2. Open and empty the entire contents of one AQNEURSA packet into a container with 40 mL of water, orange juice, or almond milk. Do not use hot liquid.
3. Stir to form a suspension.
4. Swallow the suspension immediately (within 30 minutes).
5. For doses requiring two AQNEURSA packets, repeat steps 2 to 4.
6. Discard unused AQNEURSA suspension if not administered within 30 minutes.

Use of Gastrostomy Tube (G-Tube) for Feeding Tube Administration

For patients who have a G-tube (French size 18 or larger) in place, administer AQNEURSA as follows:

1. Prepare AQNEURSA suspension immediately before administration via gastrostomy tube.
2. Obtain the required number of AQNEURSA packets for the prescribed dose (one or two packets).
3. Open and empty the entire contents of one AQNEURSA packet into a container with 40 mL of water ONLY. Do not use hot liquid.
4. Stir to form a suspension.
5. Draw up the suspension into a catheter tip syringe.
6. Administer the suspension immediately through the G-tube.
7. Flush any residual suspension in the catheter tip syringe with an additional 20 mL of water.
8. Flush the G-tube again, as needed, until no residual suspension is left in the syringe or feeding tube.
9. For doses requiring two AQNEURSA packets, repeat steps 3 to 8.
10. Discard unused AQNEURSA suspension if not administered immediately.

3 DOSAGE FORMS AND STRENGTHS

For oral suspension: 1 gram levacetylleucine as white to off-white strawberry flavored granules in a unit-dose packet.

4 CONTRAINDICATIONS

None.

5 WARNINGS AND PRECAUTIONS

5.1 Embryo-Fetal Toxicity

Based on findings from animal reproduction studies, AQNEURSA may cause embryo-fetal harm when administered during pregnancy. Administration of levacetylleucine to pregnant rats and rabbits during the period of organogenesis caused an increase in embryo-fetal death (post implantation loss/resorption) and skeletal malformations at a dose that was approximately 1.4-fold and 6-fold, respectively, the maximum recommended human dose (MRHD) of 4 g/day of levacetylleucine (based on body surface area).

The decision to continue or discontinue AQNEURSA treatment during pregnancy should consider the female’s need for AQNEURSA, the potential drug-related risks to the fetus, and the potential adverse outcomes from untreated maternal disease.

For females of reproductive potential, verify that the patient is not pregnant prior to initiating treatment with AQNEURSA. Advise females of reproductive potential to use effective contraception during treatment with AQNEURSA and for 7 days after the last dose if AQNEURSA is discontinued [see Use in Specific Populations (8.1, 8.3)].

6 ADVERSE REACTIONS

6.1 Clinical Trials Experience

Because clinical trials are conducted under widely varying conditions, adverse reaction rates observed in the clinical trials of a drug cannot be directly compared to rates in the clinical trials of another drug and may not reflect the rates observed in practice.

The safety of AQNEURSA was evaluated in Trial 1, which included a total of 60 patients with Niemann-Pick disease Type C (NPC), in a placebo-controlled, randomized, crossover trial [see Clinical Studies (14)]. The mean (SD) treatment duration of AQNEURSA was 86.2 (4.7) days (69 min, 97 max); the mean (SD) treatment duration on placebo was 87.3 (4.8) days (78 min, 113 max).

Table 2 summarizes adverse reactions that occurred in patients who were treated with AQNEURSA in Treatment Period I of Trial 1.

Table 2 Adverse Reactions that Occurred in Adult and Pediatric Patients with NPC at an Incidence of ≥5% in Treatment Period I of Trial 1
Adverse Reaction | AQNEURSA N=30 n (%) | Placebo N=30 n (%)
Upper respiratory tract infection | 5 (17) | 1 (3)
Abdominal pain | 2 (7) | 0 (0)
Dysphagia | 2 (7) | 0 (0)
Vomiting | 2 (7) | 0 (0)

Rosacea

One patient experienced an exacerbation of rosacea during Trial 1 that responded to treatment. AQNEURSA was not discontinued.

Laboratory Findings

Thrombocytopenia with platelets < 100 10^3 cells/µL was observed in four patients during Treatment Period 1, all of whom were receiving miglustat for 42 days or longer at the time of enrollment. In two of these patients, the thrombocytopenia was present at baseline. In the other two patients, the thrombocytopenia developed during the trial.

7 DRUG INTERACTIONS

7.1 Effect of Other Drugs on AQNEURSA

N-acetyl-DL-leucine and N-acetyl-D-leucine

Avoid concomitant use of AQNEURSA with N-acetyl-DL-leucine and N-acetyl-D-leucine. The D-enantiomer, N-acetyl-D-leucine, competes with levacetylleucine for monocarboxylate transporter uptake, which may reduce the levacetylleucine efficacy.

7.2 Effect of AQNEURSA on Other Drugs

P-glycoprotein (P-gp) Transporter Substrates

Monitor more frequently for P-gp substrate related adverse reactions when used concomitantly with AQNEURSA.

Levacetylleucine inhibits P-gp [see Clinical Pharmacology (12.3)]. However, the clinical significance of this finding has not been fully characterized.

8 USE IN SPECIFIC POPULATIONS

8.1 Pregnancy

Risk Summary

Based on findings from animal reproduction studies, AQNEURSA may cause embryo-fetal harm when administered during pregnancy. In animal reproduction studies, an increase in embryo-fetal death (post implantation loss/resorption), decrease in fetal body weight, and increase in external and skeletal malformations were observed in rats and rabbits when levacetylleucine was administered in pregnant rats and rabbits during the period of organogenesis. These effects were observed in rats and rabbits at the doses that were approximately 1.4-fold and 6-fold, respectively, the maximum recommended human dose (MRHD) in patients taking 4 grams of AQNEURSA per day (see Data).

There are no available data on AQNEURSA use in pregnant females to evaluate a drug-associated risk of major birth defects, miscarriage or other adverse maternal or fetal outcomes. Advise a pregnant female of the potential risk to the fetus. The decision to continue or discontinue AQNEURSA treatment during pregnancy should consider the female’s need for AQNEURSA, the potential drug-related risks to the fetus, and the potential adverse outcomes from untreated maternal disease.

The background risk of major birth defects and miscarriage for the indicated population is unknown. All pregnancies have a background risk of birth defect, miscarriage, or other adverse outcomes. In the U.S. general population, the estimated background risk of major birth defects and miscarriage in clinically recognized pregnancies is 2 to 4% and 15 to 20%, respectively.

Data

Animal Data

In a dose-range finding rat embryo-fetal development study, doses of up to 1000 mg/kg/day oral levacetylleucine were administered daily to pregnant females during organogenesis (Gestation Day [GD] 6 through GD 17). Increases in the mean number of resorptions, mean post-implantation losses and skeletal malformations (thoracic arch of the vertebra-fused thoracic arch, misaligned thoracic arch, hemicentric thoracic centrum, and misaligned thoracic centrum; vertebral column-scoliosis, and ribs-absent costal cartilage and short rib) were observed at a dose of 600 mg/kg/day, which is 1.4-fold the 4 g/day MRHD of levacetylleucine based on body surface area.

In a dose-range finding rabbit embryo-fetal development study, doses of up to 2500 mg/kg/day oral levacetylleucine were administered daily to pregnant females during organogenesis (GD 7 through GD 19). Increased embryo-fetal death (post-implantation loss/resorption), decreased fetal body weight, and increase in external (open or partially open eyes, hyperflexion of limbs) and skeletal malformations (misshapen maxillae and premaxillae, and small interparietal bones) were observed at the dose of 1250 mg/kg/day, which is 6-fold the MRHD of levacetylleucine based on body surface area.

8.2 Lactation

Risk Summary

There are no data on the presence of levacetylleucine or its metabolites in either human or animal milk, the effects on the breastfed infant or the effects on milk production. The developmental and health benefits of breastfeeding should be considered along with the mother’s clinical need for AQNEURSA and any potential adverse effects on the breastfed infant from levacetylleucine or from the underlying maternal condition.

8.3 Females and Males of Reproductive Potential

AQNEURSA may cause embryo-fetal harm when administered to a pregnant female [see Use in Specific Populations (8.1)].

Pregnancy Testing

For a female of reproductive potential, verify that the patient is not pregnant prior to initiating treatment with AQNEURSA.

Contraception

Females

Advise a female of reproductive potential to use effective contraception during treatment and for 7 days after the last dose if AQNEURSA is discontinued.

8.4 Pediatric Use

The safety and effectiveness of AQNEURSA for the treatment of NPC have been established in 23 pediatric patients weighing ≥15 kg in Trial 1. Use of AQNEURSA for this indication is supported by evidence from one adequate and well-controlled study in adults and pediatric patients weighing ≥15 kg with additional pharmacokinetic data from 40 adults and 17 pediatric patients who participated in two open-label studies [see Clinical Studies (14) and Clinical Pharmacology (12.3)]. The safety and effectiveness of AQNEURSA have not been established in pediatric patients weighing <15 kg.

8.5 Geriatric Use

NPC is largely a disease of pediatric and young adult patients. Clinical studies of AQNEURSA did not include sufficient numbers of patients 65 years of age and older to determine whether they respond differently from younger adult patients.

11 DESCRIPTION

AQNEURSA (levacetylleucine) for oral suspension contains the drug substance levacetylleucine, a modified amino acid. Levacetylleucine is slightly soluble in aqueous solutions. The chemical name is 2-acetamido-4-methylpentanoic acid. The empirical formula is C8H15NO3 and the molecular weight is 173.21. The chemical structure is:

Each packet of AQNEURSA granules contains 1 gram levacetylleucine and the inactive ingredients hypromellose, isomalt and strawberry flavor.

12 CLINICAL PHARMACOLOGY

12.1 Mechanism of Action

The distinct molecular target for levacetylleucine in the treatment of NPC is unknown.

12.2 Pharmacodynamics

Clinical pharmacodynamic studies have not been conducted for levacetylleucine.

A relationship was not observed between increasing levacetylleucine exposure and clinical efficacy. The time course of pharmacodynamic response is unknown.

12.3 Pharmacokinetics

Levacetylleucine pharmacokinetic parameters at steady state are presented as mean (SD) unless otherwise specified. Levacetylleucine maximum concentration (Cmax) and area under the curve from time 0 to 24 hours (AUC0-24hrs) were 8.3 (3.3) µg/mL and 33.2 (12.5) h*μg/mL.

No levacetylleucine accumulation occurs after repeated administration.

Absorption

Levacetylleucine time to Cmax (Tmax) is 1 hour (ranging from 0.5 to 2.5 hours).

Distribution

Levacetylleucine apparent (oral) volume of distribution (VSS/F) is 253 (125) L.

Elimination

Levacetylleucine estimated half-life is around 1 hour and the apparent (oral) clearance is 139 (59) L/h.

Metabolism

Levacetylleucine is metabolized into acetate and L-leucine by ubiquitously expressed enzymes, which are used endogenously in catabolic and metabolic pathways. Cytochrome P450 enzymes are not involved in the metabolism of levacetylleucine.

Specific Populations

No clinically significant differences in pharmacokinetics of levacetylleucine were observed based on age (range 5 to 67 years), gender (female 45.5%, male 54.5%), or race/ethnicity (White 91%, Asian 4%, Other or not specified 5%). The effect of renal impairment, hepatic impairment, or pregnancy on levacetylleucine pharmacokinetics is unknown.

Body Weight

The volume of distribution and clearance of levacetylleucine increases with increasing body weight (20.5 kg to 98.4 kg), but these effects on pharmacokinetics are minimized by the recommended weight-based dosing.

Drug Interaction Studies

In Vitro Studies

Cytochrome P450 (CYP450) enzymes: Levacetylleucine does not inhibit CYP 1A2, 2B6, 2C8, 2C9, 2C19, 2D6, or 3A4 and does not induce CYP 1A2, 2B6, and or 3A4.

Transporter Systems

Levacetylleucine is a substrate of organic anion transporter (OAT)1 and OAT3, but not organic cation transporter (OCT)2, breast cancer resistance protein (BCRP), or P-glycoprotein (P-gp). Levacetylleucine inhibits P-gp, BCRP, bile salt export pump (BSEP), OAT1 and OAT3, but does not inhibit organic anion transporting polypeptide (OATP)1B1 and OATP1B3.

13 NONCLINICAL TOXICOLOGY

13.1 Carcinogenesis, Mutagenesis, Impairment of Fertility

Carcinogenesis

Animal studies to evaluate the carcinogenic potential of levacetylleucine have not been conducted.

Mutagenesis

Levacetylleucine was not mutagenic or clastogenic in a battery of in vitro and in vivo assays including bacterial reverse mutation (Ames), chromosomal aberration (in human lymphocytes) and mouse micronucleus assays.

Impairment of Fertility

Animal studies to evaluate effects of levacetylleucine on fertility have not been conducted.

14 CLINICAL STUDIES

The safety and efficacy of AQNEURSA for the treatment of NPC were evaluated in a randomized, double-blind, placebo-controlled, two-period crossover study (NCT05163288) that evaluated the efficacy of AQNEURSA in 60 patients. To be eligible for the study, patients had to be aged 4 years or older with a confirmed diagnosis of NPC. Patients were required to have at least mild disease-related neurological symptoms.

Patients were assessed over a 2-week baseline period. Patients were then randomized in a 1:1 ratio to one of the two treatment sequences:

- Treatment Sequence 1 (N=30): AQNEURSA in Treatment Period I, followed by immediate crossover to placebo in Treatment Period II
- Treatment Sequence 2 (N=30): placebo in Treatment Period I, followed by immediate crossover to AQNEURSA in Treatment Period II.

AQNEURSA and placebo were administered orally with or without food for 12 weeks in each period.

Patients aged ≥13 years received 4 gram per day (as 2 gram morning dose, 1 gram afternoon dose, and 1 gram evening dose). The AQNEURSA dosage in pediatric patients under 13 years was based on patient’s body weight [see Dosage and Administration (2.2)].The approved dosage regimen is based on body weight and not age. Fifty-nine patients (98%) completed the study and received both placebo and AQNEURSA. One patient withdrew based on healthcare provider decision during AQNEURSA treatment.

Of the 60 randomized patients (37 adults and 23 pediatric patients), 27 were female and 33 were male. The median age at treatment initiation was 25 years (range: 5 to 67 years). 90% of the patients were White, 3% Asian, and 7% Other. The majority of the patients (n=51, 85%) received miglustat treatment prior to randomization and during the trial.

The primary efficacy outcome was assessed using a modified version of the Scale for Assessment and Rating of Ataxia (SARA), referred to as the functional SARA (fSARA). The SARA is a clinical assessment tool that assesses gait, stability, speech, and upper and lower limb coordination across 8 individual domains. The fSARA consists only of gait, sitting, stance, and speech disturbance domains of the original SARA with modifications to the scoring responses. Each domain was rescored from 0 to 4, where 0 is the best neurological status and 4 the worst, with a total score ranging from 0 to 16.

The fSARA score was assessed at baseline, 6 weeks, 12 weeks (the end of Period I), 18 weeks, and 24 weeks (the end of Period II). The estimated mean fSARA total score was 5.1 when patients were treated with AQNEURSA and 5.6 when patients were treated with placebo. The estimated treatment difference for the fSARA total score was -0.4 (95% CI: -0.7, -0.2) (Table 3).

Table 3 Summary of fSARA Efficacy Results
Variable | fSARA Total Score
Variable | Treatment Sequence 1:; AQNEURSA - Placebo | Treatment Sequence 2:; Placebo - AQNEURSA
Baseline | N=30 | N=30
Mean (SD) | 5.2 (3.0) | 6.3 (3.3)
Period I | N=29 | N=30
Mean (SD) | 4.5 (2.6) | 6.0 (3.4)
Period II | N=28 [Two patients did not have an assessment at the end of Period II (week 24).] | N=30
Mean (SD) | 5.1 (2.8) | 5.6 (3.1)
Estimated Mean fSARA Score (SE) by Treatment
AQNEURSA | 5.1 (0.1)
Placebo | 5.6 (0.1)
Treatment Difference (95% CI) | -0.4 (-0.7, -0.2) [Two-sided p-value <0.001]
CI = confidence interval; SD = standard deviation; SE = standard error.

Patients who received AQNEURSA in Period I followed by placebo in Period II (Treatment Sequence 1) showed a greater improvement in the fSARA score in Period I with a mean change from baseline of -0.5 (SD 1.2), compared to Period II with a mean change from baseline of 0 (1.5). Similarly, patients who received placebo in Period I followed by AQNEURSA in Period II (Treatment Sequence 2) experienced greater improvement in the fSARA score while receiving AQNEURSA in Period II with a mean change of -0.7 (0.9), compared to a mean change of -0.3 (0.9) in Period I.

Figure 1 Mean (+/- standard error) plot of the fSARA total score by time and treatment sequence

Results on the fSARA were supported by consistent results demonstrated on the original SARA.

16 HOW SUPPLIED/STORAGE AND HANDLING

How Supplied

AQNEURSA (levacetylleucine) for oral suspension is supplied as white to off-white granules in a unit-dose multi-layer aluminum/polyethylene packet. Each packet contains 1.7 gram white to off-white granules, equivalent to 1 gram levacetylleucine.

NDC 83853-101-01: Carton containing 28 unit-dose packets

Storage and Handling

Store AQNEURSA at room temperature between 20°C to 25°C (68°F to 77°F); excursion permitted between 15°C to 30°C (59°F to 86°F) [see USP Controlled Room Temperature].

17 PATIENT COUNSELING INFORMATION

Advise the patient and/or caregiver to read the FDA-approved patient labeling (Instructions for Use).

Embryo-Fetal Toxicity

AQNEURSA may cause embryo-fetal harm. Advise a pregnant female of the potential risk to the fetus. Advise a female of reproductive potential and caregiver to inform their healthcare provider of a known or suspected pregnancy [see Warnings and Precautions (5.1) and Use in Specific Populations (8.1)]. Advise a female of reproductive potential to use effective contraception during treatment and for 7 days after the last dose if AQNEURSA is discontinued [see Use in Specific Populations (8.1, 8.3)].

Distributed by: IntraBio Inc., Austin TX 78701

AQNEURSA is a trademark of IntraBio.

INSTRUCTIONS FOR USE

AQNEURSA [ak nur' sah]

(levacetylleucine)

for oral suspension

This Instructions for Use contains information on how to prepare and take or give AQNEURSA oral suspension. Read this Instructions for Use before you prepare and take or give the first dose of AQNEURSA oral suspension and each time you get a refill. There may be new information. This Instructions for Use does not take the place of talking to you or your child’s healthcare provider about your or your child’s medical condition or treatment.

Important Information You Need to Know Before Taking or Giving AQNEURSA Oral Suspension

- Take or give AQNEURSA oral suspension exactly as instructed by your healthcare provider.
- Take or give AQNEURSA oral suspension with or without food.
- AQNEURSA oral suspension can be taken or given by mouth or through a gastrostomy tube (G-tube) feeding tube (French size 18 or larger).
- Do not use hot liquid with AQNEURSA oral suspension.
- For instructions on disposing of expired AQNEURSA packets or unused AQNEURSA oral suspension, see the end of this Instructions for Use.

Supplies Needed to Prepare and Take or Give AQNEURSA Oral Suspension

Gather the following supplies on a clean flat surface:

- the number of AQNEURSA packets needed for your prescribed dose
- a clean spoon
- a container
- a measuring cup from your pharmacist
- 40 mL of water, orange juice, or almond milk
- catheter tip syringe (if giving AQNEURSA oral suspension through G-tube)

Preparing AQNEURSA Oral Suspension

Step 1: Wash and dry your hands.

Step 2: Open and empty the entire contents of 1 AQNEURSA packet into a container with 40 mL of:

- water, orange juice or almond milk (when taken by mouth), or
- water only when given through a G-tube.

Do not use hot liquid.

Step 3: Stir to form the suspension.

Note:

- Go to Step 4 for taking AQNEURSA oral suspension by mouth, or
- Go to Step 6 for giving AQNEURSA oral suspension through a gastrostomy tube (G-tube).

Taking AQNEURSA Oral Suspension by Mouth

Step 4: Swallow AQNEURSA oral suspension right away (within 30 minutes).

Throw away (dispose of) unused AQNEURSA oral suspension if not taken within 30 minutes.

Step 5: If your prescribed dose requires 2 AQNEURSA packets, repeat Steps 1 through 4.

Giving AQNEURSA Oral Suspension Through a Gastrostomy Tube (G-tube)

- Give AQNEURSA oral suspension through a G-tube that is a French size of 18 or larger.
- Follow Steps 1 through 3 to prepare AQNEURSA oral suspension.

Note: Only use 40 mL of water for preparing AQNEURSA oral suspension when given through G-tube.

Step 6: Draw up the prepared AQNEURSA oral suspension into a catheter tip syringe.

Step 7: Inject the AQNEURSA oral suspension through the G-tube right away.

Throw away (dispose of) unused AQNEURSA oral suspension if not given right away.

Step 8: Refill the syringe with an additional 20 mL water.

Step 9: Flush the G-tube with water, until no remaining AQNEURSA oral suspension is seen in the syringe or G-tube.

Step 10: If your prescribed dose requires 2 AQNEURSA packets, follow Steps 1 through 3 to prepare the AQNEURSA oral suspension, then repeat Steps 6 through 9.

Storing AQNEURSA

- Store AQNEURSA at room temperature between 68°F to 77°F (20°C to 25°C).
- Keep AQNEURSA oral suspension and all medicines out of reach of children.

Disposing of Expired AQNEURSA Packets or Unused AQNEURSA Oral Suspension

Throw away (dispose of) expired AQNEURSA packets or unused AQNEURSA oral suspension following the steps below:

- Mix medicine with a substance such as dirt, cat litter, or used coffee grounds.
- Place the mixture in a container such as a sealed plastic bag.
- Throw away (dispose of) the container in your household trash.

Distributed by: IntraBio Inc., Austin, TX 78701

This Instructions for Use has been approved by the U.S. Food and Drug Administration.

Issued: 9/2024